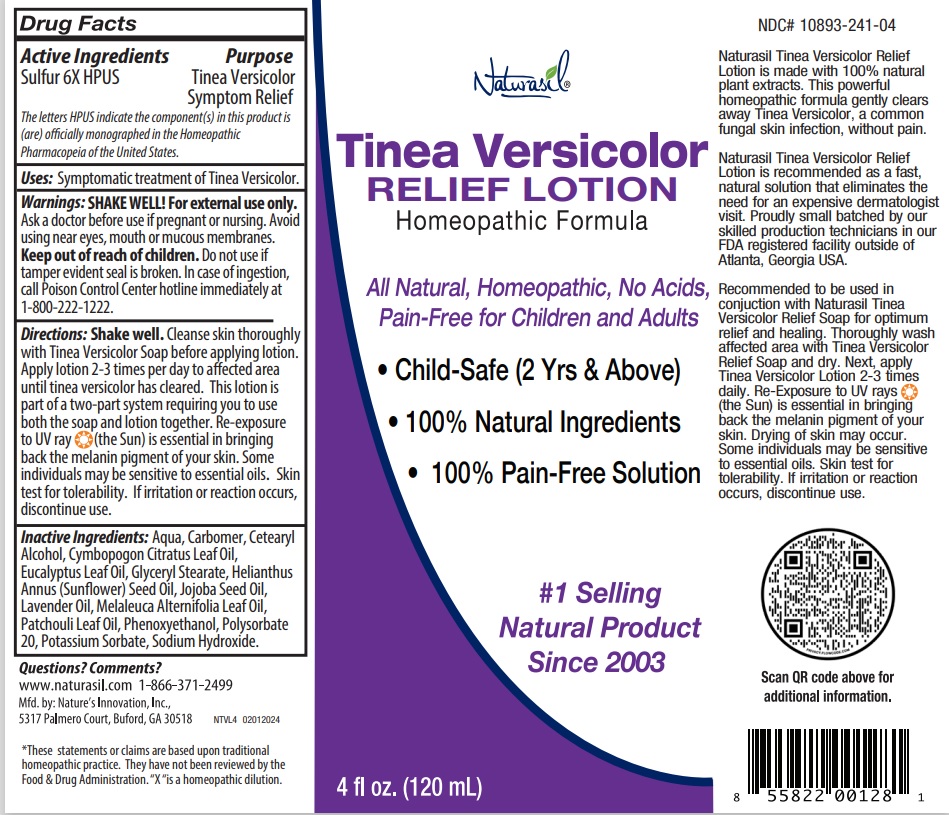 DRUG LABEL: Naturasil Tinea Versicolor  Relief
NDC: 10893-241 | Form: LOTION
Manufacturer: Nature's Innovation, Inc.
Category: homeopathic | Type: HUMAN OTC DRUG LABEL
Date: 20240229

ACTIVE INGREDIENTS: SULFUR 6 [hp_X]/120 mL
INACTIVE INGREDIENTS: WATER; CARBOMER HOMOPOLYMER, UNSPECIFIED TYPE; CETOSTEARYL ALCOHOL; WEST INDIAN LEMONGRASS OIL; EUCALYPTUS OIL; GLYCERYL MONOSTEARATE; SUNFLOWER OIL; JOJOBA OIL; LAVENDER OIL; TEA TREE OIL; POGOSTEMON HEYNEANUS LEAF OIL; PHENOXYETHANOL; POLYSORBATE 20; POTASSIUM SORBATE; SODIUM HYDROXIDE

Naturasil Tinea Versicolor RELIEF LOTION

Active Ingredients

Sulfur 6X HPUS

The letters HPUS indicate the component(s) in this product is (are) officially monographed in the Homeopathic Pharmacopeia of the United States.

Purpose

Tinea Versicolor Symptom Relief

Uses:

Symptomatic treatment of Tinea Versicolor.

Warnings:

SHAKE WELL! For external use only.
Ask a doctor before use if pregnant or nursing. Avoid using near eyes, mouth or mucous membranes.

Keep out of reach of children. Do not use if tamper evident seal is broken. In case of ingestion, call Poison Control Center hotline immediately at 1-800-222-1222.

Directions:

Shake well. Cleanse skin thoroughly with Tinea Versicolor Soap before applying lotion. Apply lotion 2-3 times per day to affected area until tinea versicolor has cleared. This lotion is part of a two-part system requiring you to use both the soap and lotion together. Re-exposure to UV ray (the sun) is essential in bringing back the melanin pigment of your skin. Some individuals may be sensitive to essential oils. Skin test for tolerability. If irritation or reaction occurs, discontinue use.

Inactive Ingredients:

Aqua, Carbomer, Cetearyl Alcohol, Cymbopogon Citratus Leaf Oil, Eucalyptus Leaf Oil, Glyceryl Stearate, Helianthus Annus (Sunflower) Seed Oil, Jojoba Seed Oil, Lavender Oil, Melaleuca Alternifolia Leaf Oil, Patchouli Leaf Oil, Phenoxyethanol, Polysorbate 20, Potassium Sorbate, Sodium Hydroxide.

Homeopathic Formula

All Natural, Homeopathic, No Acids, Pain-Free for Children and Adults

• Child-Safe (2 Yrs & Above)
• 100% Natural Ingredients
• 100% Pain-Free Solution

#1 Selling Natural product Since 2003

Naturasil Tinea Versicolor Relief Lotion is made with 100% natural plant extracts. This powerful homeopathic formula gently clears
away Tinea Versicolor, a common fungal skin infection, without pain.

Naturasil Tinea Versicolor Relief Lotion is recommended as a fast, natural solution that eliminates the need for an expensive dermatologist visit. Proudly small batched by our skilled production technicians in our FDA registered facility outside of Atlanta, Georgia USA.

Recommended to be used in conjuction with Naturasil Tinea Versicolor Relief Soap for optimum relief and healing. Thoroughly wash affected area with Tinea Versicolor Relief Soap and dry. Next, apply Tinea Versicolor Lotion 2-3 times daily. Re-Exposure to UV rays (the Sun) is essential in bringing back the melanin pigment of your skin. Drying of skin may occur. Some individuals may be sensitive to essential oils. Skin test for
tolerability. If irritation or reaction occurs, discontinue use.

Questions? Comments?

www.naturasil.com 1-866-371-2499

Mfd. by: Nature’s Innovation, Inc.,
5317 Palmero Court, Buford, GA 30518

*These statements or claims are based upon traditional homeopathic practice. They have not been reviewed by the Food & Drug Administration. “X “is a homeopathic dilution.